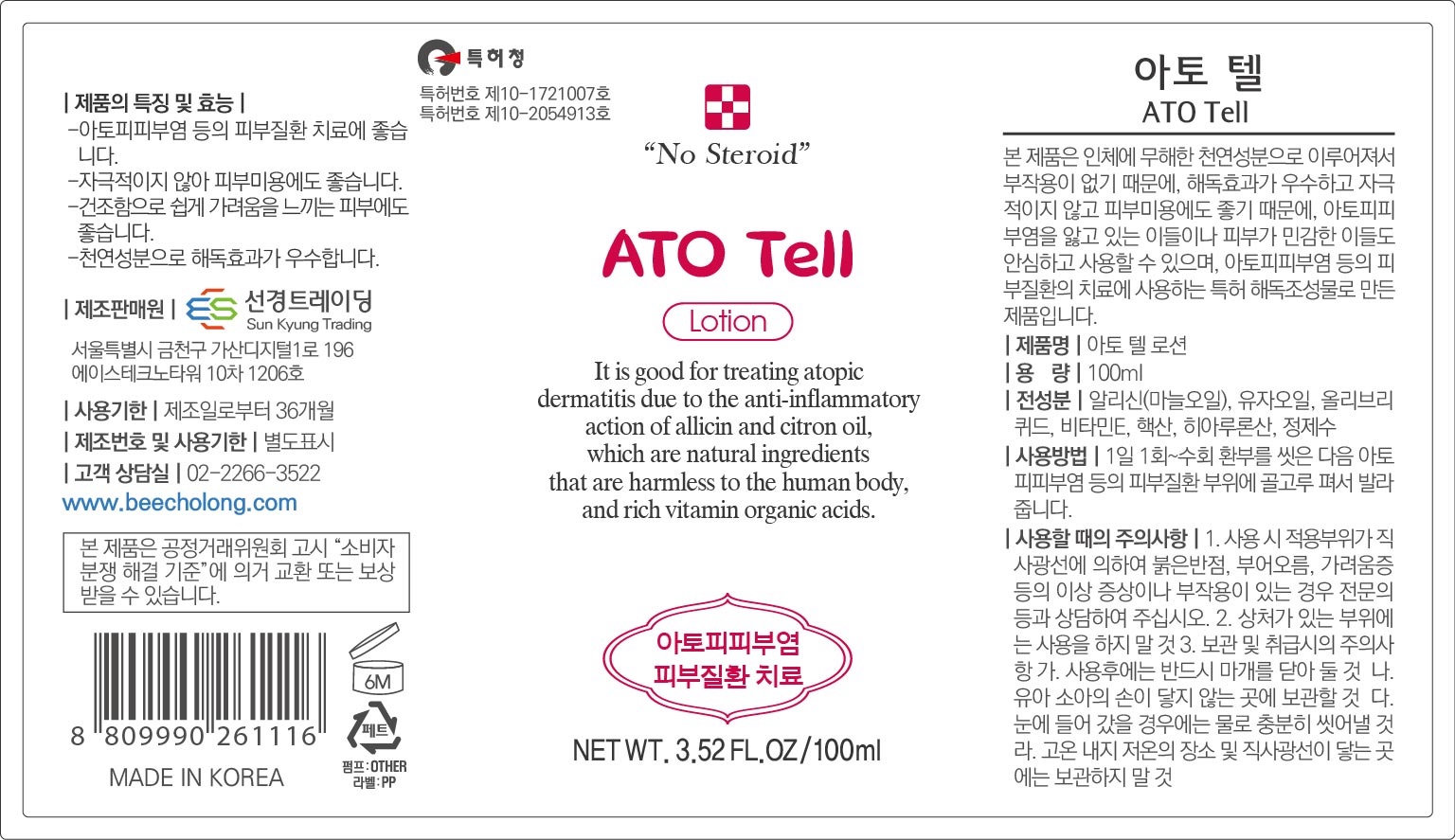 DRUG LABEL: ATO Tell
NDC: 82994-0002 | Form: LIQUID
Manufacturer: sunkyung trading
Category: otc | Type: HUMAN OTC DRUG LABEL
Date: 20230406

ACTIVE INGREDIENTS: MENTHOL 1.2 g/100 mL; GARLIC OIL 7.5 g/100 mL
INACTIVE INGREDIENTS: ALLANTOIN; BUTYLENE GLYCOL; WATER

ACTIVE INGREDIENT

menthol, garlic oil

PURPOSE

digestion

Keep out of reach of children

INDICATIONS AND USAGE

shake the container for 2 to 3 times before use, apply it evenly

WARNINGS

■ if following abnormal symptoms occurs after use , stop use and consult with a skin specialist

red specks, swelling, itching

■ don’t use on the part where there is injury, eczema, or dermatitis

Keep out of reach of children

■ if swallowed, get medical help or contact a person control center immediately

INACTIVE INGREDIENT

purified water
Batylene Glycol
allantoin
SODIUMHYALURONATE
Solubiliser
1.2Hexanediol
Vitamin E
Carbomer
DisodiumEDTA
TEA TREE oil
citrus junos seed oil
Avandula Angustifolia(Lavander) oil

DOSAGE AND ADMINISTRATION

for external use only